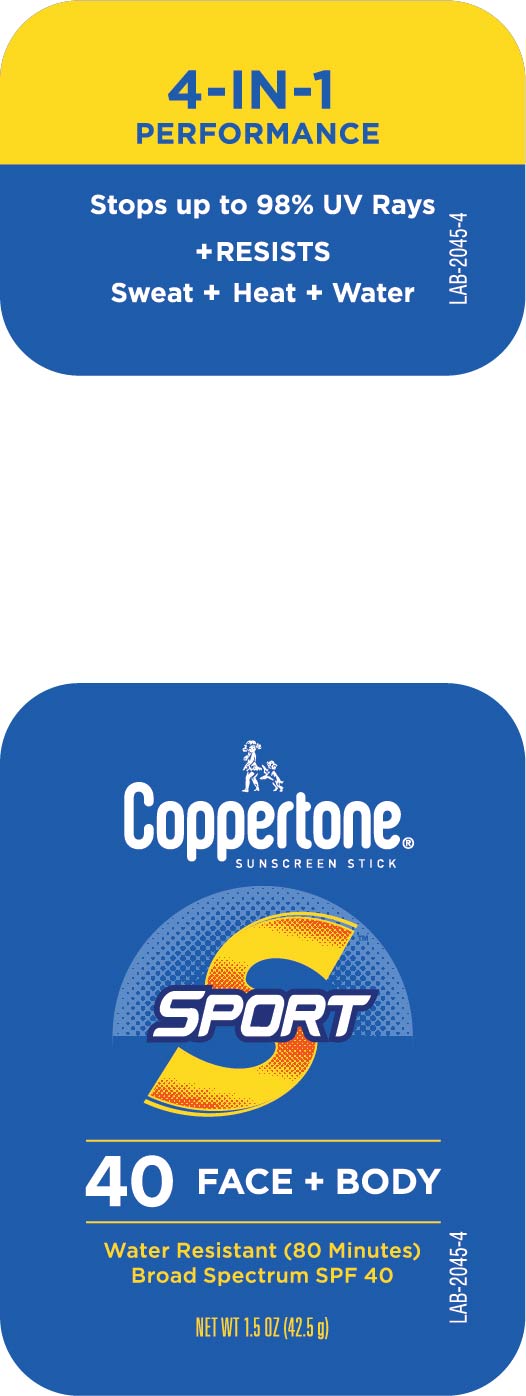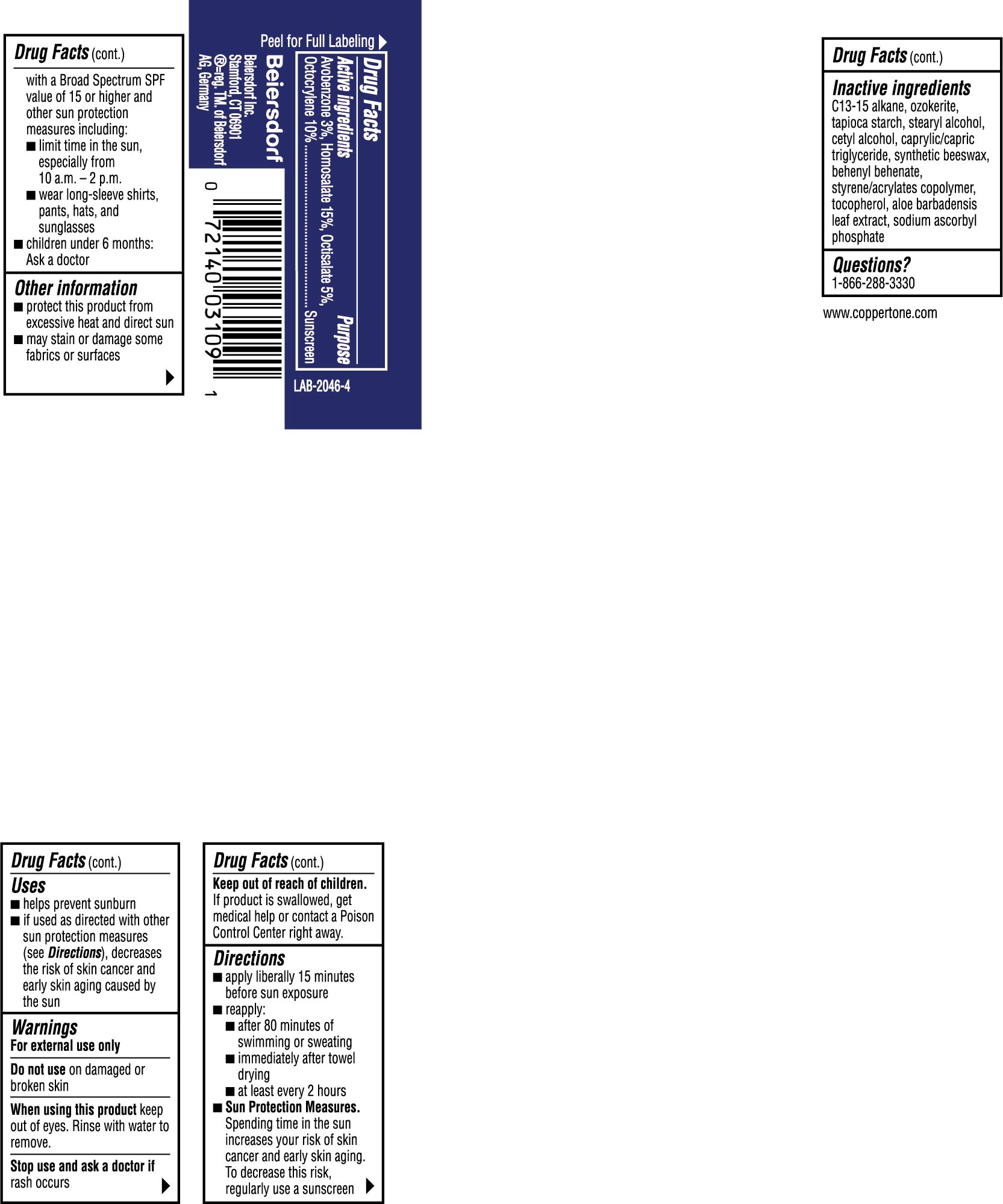 DRUG LABEL: Coppertone Sport Sunscreen SPF 40
NDC: 66800-4118 | Form: STICK
Manufacturer: Beiersdorf Inc
Category: otc | Type: HUMAN OTC DRUG LABEL
Date: 20251231

ACTIVE INGREDIENTS: OCTOCRYLENE 10 g/100 g; OCTISALATE 5 g/100 g; AVOBENZONE 3 g/100 g; HOMOSALATE 15 g/100 g
INACTIVE INGREDIENTS: MEDIUM-CHAIN TRIGLYCERIDES; STARCH, TAPIOCA; SYNTHETIC BEESWAX; STYRENE/ACRYLAMIDE COPOLYMER (MW 500000); BEHENYL BEHENATE; TOCOPHEROL; C13-15 ALKANE; CERESIN; STEARYL ALCOHOL; CETYL ALCOHOL; ALOE VERA LEAF; SODIUM ASCORBYL PHOSPHATE

Sport Stick Sunscreen SPF 40

Active ingredients

Avobenzone 3%, Homosalate 15%, Octisalate 5%, Octocrylene 10%

Purpose

Sunscreen

Uses

■ helps prevent sunburn

■ if used as directed with other sun protection measures (see Directions), decreases the risk of skin cancer and early skin aging caused by the sun

Warnings

For external use only

Do not useon damaged or broken skin

WHEN USING

When using this productkeep out of eyes. Rinse with water to remove.

Stop use and ask a doctor ifrash occurs

Keep out of reach of children.If product is swallowed, get medical help or contact a Poison Control Center right away.

Directions

■ apply liberally 15 minutes before sun exposure

■ reapply:

■ after 80 minutes of swimming or sweating

■ immediately after towel drying

■ at least every 2 hours

■ Sun Protection Measures.Spending time in the sun increases your risk of skin cancer and early skin aging. To decrease this risk, regularly use a sunscreen with a Broad Spectrum SPF value of 15 or higher and other sun protection measures including:

■ limit time in the sun, especially from 10 a.m. – 2 p.m.

■ wear long-sleeve shirts, pants, hats, and sunglasses

■ children under 6 months: Ask a doctor

Other information

■ protect this product from excessive heat and direct sun

■ may stain or damage some fabrics or surfaces

Inactive ingredients

C13-15 alkane, ozokerite, tapioca starch, stearyl alcohol, cetyl alcohol, caprylic/capric triglyceride, synthetic beeswax, behenyl behenate, styrene/acrylates copolymer, tocopherol, aloe barbadensis leaf extract, sodium ascorbyl phosphate

Questions?

1-866-288-3330

PACKAGE LABEL

4-IN-1 Performance

Stops up to 98% UV Rays

+ Resists

Sweat + Heat + Water

Coppertone®Sunscreen Stick

Sport

40 Face + Body

Water Resistant (80 Minutes)

Broad Spectrum SPF 40

NET WT 1.5 OZ (42.5 g)